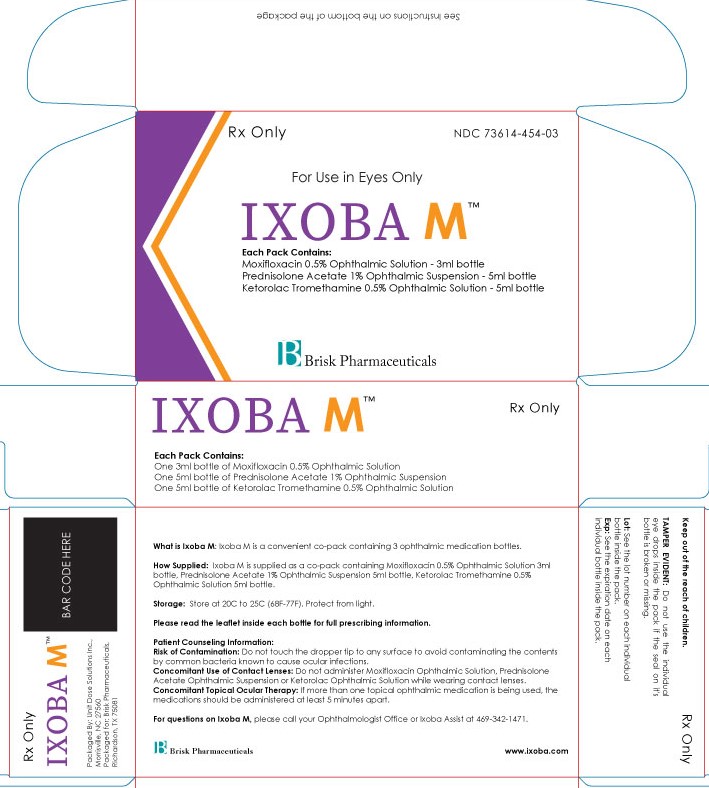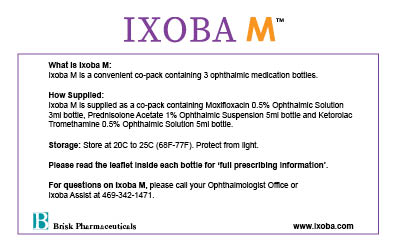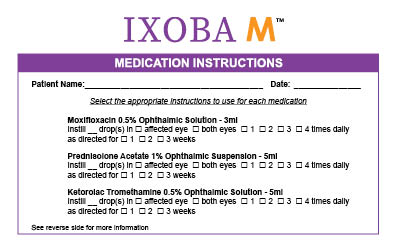 DRUG LABEL: IXOBA M
NDC: 73614-454 | Form: KIT | Route: OPHTHALMIC
Manufacturer: Brisk Pharmaceuticals, Inc.
Category: prescription | Type: HUMAN PRESCRIPTION DRUG LABEL
Date: 20211103

ACTIVE INGREDIENTS: KETOROLAC TROMETHAMINE 5 mg/1 mL; PREDNISOLONE ACETATE 10 mg/1 mL; MOXIFLOXACIN HYDROCHLORIDE MONOHYDRATE 5 mg/1 mL
INACTIVE INGREDIENTS: WATER; EDETATE DISODIUM; SODIUM CHLORIDE; HYDROCHLORIC ACID; BENZALKONIUM CHLORIDE; SODIUM HYDROXIDE; POLYSORBATE 80; SODIUM CITRATE; EDETATE DISODIUM; WATER; SODIUM BISULFITE; SODIUM CHLORIDE; BENZALKONIUM CHLORIDE; BORIC ACID; HYPROMELLOSES; BORIC ACID; HYDROCHLORIC ACID; SODIUM CHLORIDE; SODIUM HYDROXIDE; WATER

IXOBA M

DESCRIPTION

Rx Only

NDC 73614-454-03

For Use in Eyes Only

IXOBA M

Each Pack Contains:

Moxifloxacin 0.5% Ophthalmic Solution - 3ml

Ketorolac 0.5% Ophthalmic Solution - 5ml

Prednisolone Acetate 1% Ophthalmic Suspension - 5ml

Brisk Pharmaceuticals

DESCRIPTION

See Instructions on the bottom of the package

What is Ixoba M used for: Ixoba M is a convenient pack containing 3 ophthalmic medication bottles.

How Supplied: Ixoba M is supplied as a co-pack containing Moxifloxacin 0.5% Ophthalmic Suspension 3ml bottle, Ketorolac 0.5% Ophthalmic Suspension 5ml bottle, Prednisolone Acetate 1% Ophthalmic Suspen-sion 5ml bottle.

Storage: Store at 20C to 25C (68F-77F). Protect from light.

Please read the leaflet inside each bottle for ‘full prescribing information’ about that medication.

Patient Counseling Information:

Risk of Contamination: Do not touch the dropper tip to any surface to avoid contaminating the contents by common bacteria known to cause ocular infections.

Concomitant Use of Contact Lenses: Do not administer Moxifloxacin Ophthalmic Suspension, Ketorolac Ophthalmic Suspension or Prednisolone Acetate Ophthalmic Suspension while wearing contact lenses.

Concomitant Topical Ocular Therapy: If more than one topical ophthalmic medication is being used, the medications should be administered at least 5 minutes apart.

For questions on Ixoba M, please call your Ophthalmologist Office or Ixoba Assist at 469-342-1471.

DESCRIPTION

Keep out of the reach of children.

TAMPER EVIDENT: Do not use the individual eye drops inside the pack if the seal on its carton is broken or missing.

Lot: See the lot number on each individual bottle inside the pack.

Exp: See the expiration date on each individual bottle inside the pack.

Packaged By: Unit Dose Solutions Inc., Morrisville, NC 27560

Packaged for: Brisk Pharmaceuticals, Dallas, TX 75217